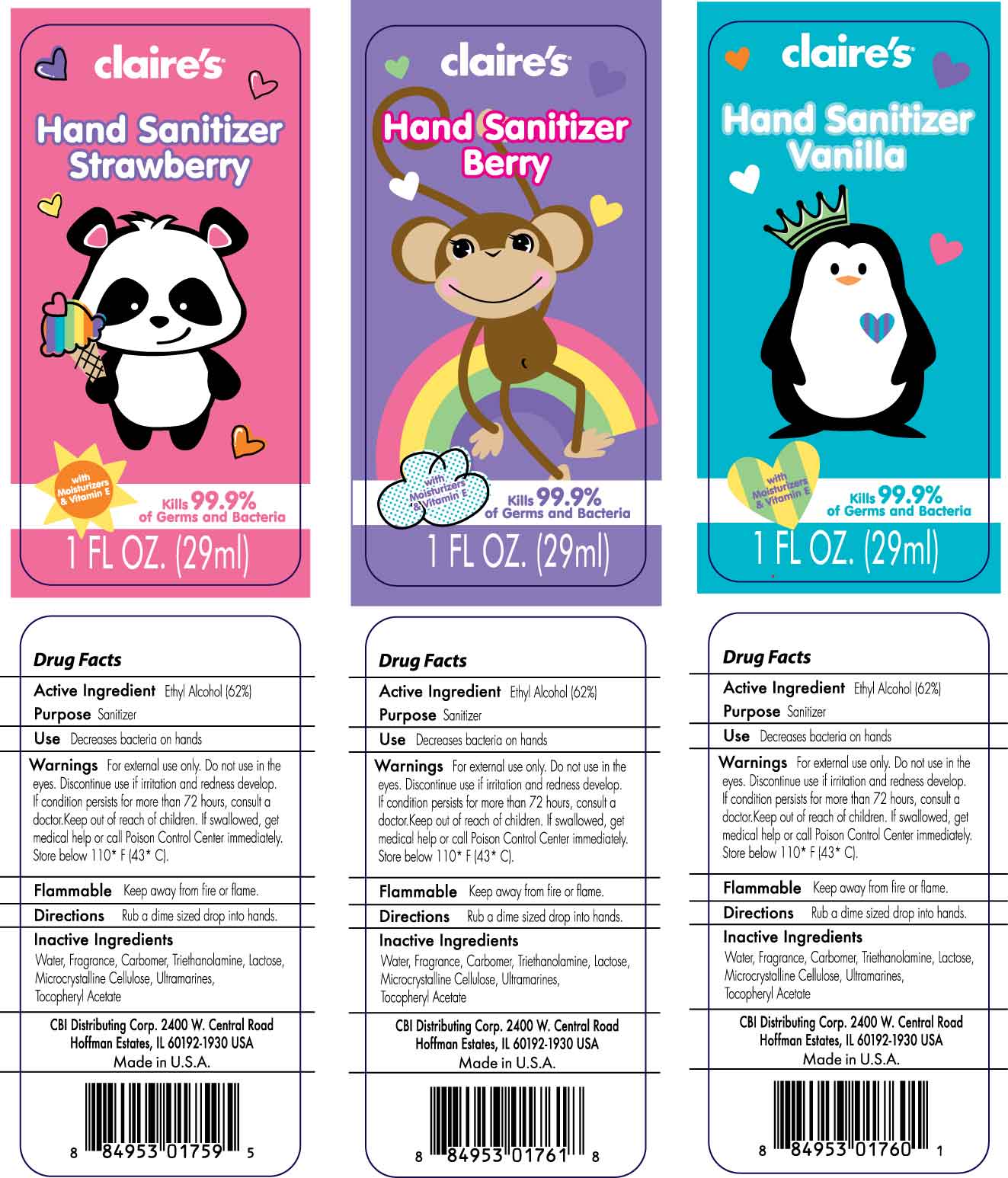 DRUG LABEL: CLAIRES
NDC: 10827-0002 | Form: GEL
Manufacturer: Yusef Manufacturing Laboratories, LLC
Category: otc | Type: HUMAN OTC DRUG LABEL
Date: 20100215

ACTIVE INGREDIENTS: ALCOHOL 0.62 g/1 g
INACTIVE INGREDIENTS: WATER; CARBOMER HOMOPOLYMER TYPE C; TROLAMINE; LACTOSE; CELLULOSE, MICROCRYSTALLINE; FERRIC OXIDE RED; (PHTHALOCYANINATO(2-)) COPPER

Claire's Hand Sanitizer (Berry, Vanilla, Strawberry)

Use Decreases bacteria on hands

WARNINGS

Warnings For external use only. Do not use in the eyes. Discontinue use if irritation and redness develop. If condition persists more than 72 hours, consult a doctor. Keep out of reach of children. If swallowed, get medical help or call Poison Control Center immediately. Store below 110 F (43 C).

Flammable Keep away from fire or flame.

Directions Rub a dime size drop into hands.

INACTIVE INGREDIENT

Inactive Ingredients Water, Fragrance, Carbomer, Triethanolamine, Lactose, Microcrystalline Cellulose, Ultramarines, Tocopheryl Acetate

CBI Distributing Corp. 2400 W. Central Road
Hoffman Estates, IL 60192-1930 U.S.A.

Made in U.S.A.

PACKAGE LABEL

Enter section text here